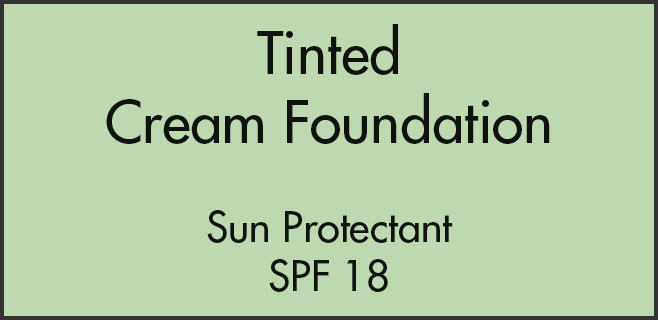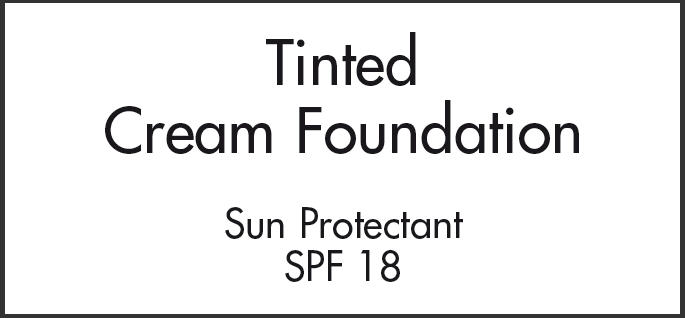 DRUG LABEL: BIO BEAUTY BIO DEFENSE 
NDC: 52424-0001 | Form: CREAM
Manufacturer: LIBINVEST
Category: otc | Type: HUMAN OTC DRUG LABEL
Date: 20100618

ACTIVE INGREDIENTS: OCTINOXATE 7.5 g/100 mL; TITANIUM DIOXIDE 8 g/100 mL

Tinted
Cream Foundation

ACTIVE INGREDIENT

PURPOSE

ACTIVE INGREDIENTS
OCTINOXATE 7.5% | Sunscreen
TITANIUM DIOXIDE 8.0% | Sunscreen

USES

Use as a foundation, helps prevent sunburn, higher SPF gives more sunburn protection.

WARNINGS

For external use only. Not to be swallowed. Avoid contact with the eyes.

Stop use and ask doctor if rash develops and lasts.

Keep out of reach of children.

DIRECTIONS

Use in place of your normal foundation.

INACTIVE INGREDIENTS

WATER, GLYCERYL STEARATE/ISOPROPYLENE GLYCOL STEARATE/GLYCERYLISOSTEARATE/OLETH-25/CETETH-25, ISODECETH-6, OLETH-10, ALUMINUM STEARATE, ALUMINA, SIMETHICONE, PROPYLENE GLYCOL DIPELARGONATE, METHYL METHACRYLATE CROSSPOLYMER, OCTYLDODECYL MYRISTATE, PALMITOYL PROLINE and MAGNESIUM PALMITOYL GLUTAMATE and SODIUM PALMITOYL SARCOSINATE, IRON OXIDES, HYDROXYETHYL ACRYLATE/SODIUM ACRYLOLDIMETHYL TAURATE COPOLYMER, SQUALANE, POLYSORBATE 60, BENZOPHENONE-3, GLYCERYL STEARATE and BEHENYL LAURYL MYRISTYL CETYL ALCOHOL and PALMITIC STEARIC ACID and LECITHIN, MAGNESIUM ALUMINUM SILICATE, BUTYROSPERMUM PARKII (SHEA BUTTER), CETYL ALCOHOL, PHENOXYETHANOL, METHYLPARABEN, ETHYLPARABEN, PROPYLPARABEN, BUTYLPARABEN, ISOBUTYLPARABEN, FRAGRANCE, TOCOPHERYL ACETATE, GUM XANTHAN, ALLANTION, METHYLISOTHIAZOLINONE.

Distributed by Primo Derma, Inc. Santa Ana, CA 92705
Tel: ++001-714-560 0111

PRINCIPAL DISPLAY PANEL - 50 ml Label

Tinted
Cream Foundation

Sun Protectant
SPF 18

PRINCIPAL DISPLAY PANEL - 150 ml Label

Tinted
Cream Foundation

Sun Protectant
SPF 18